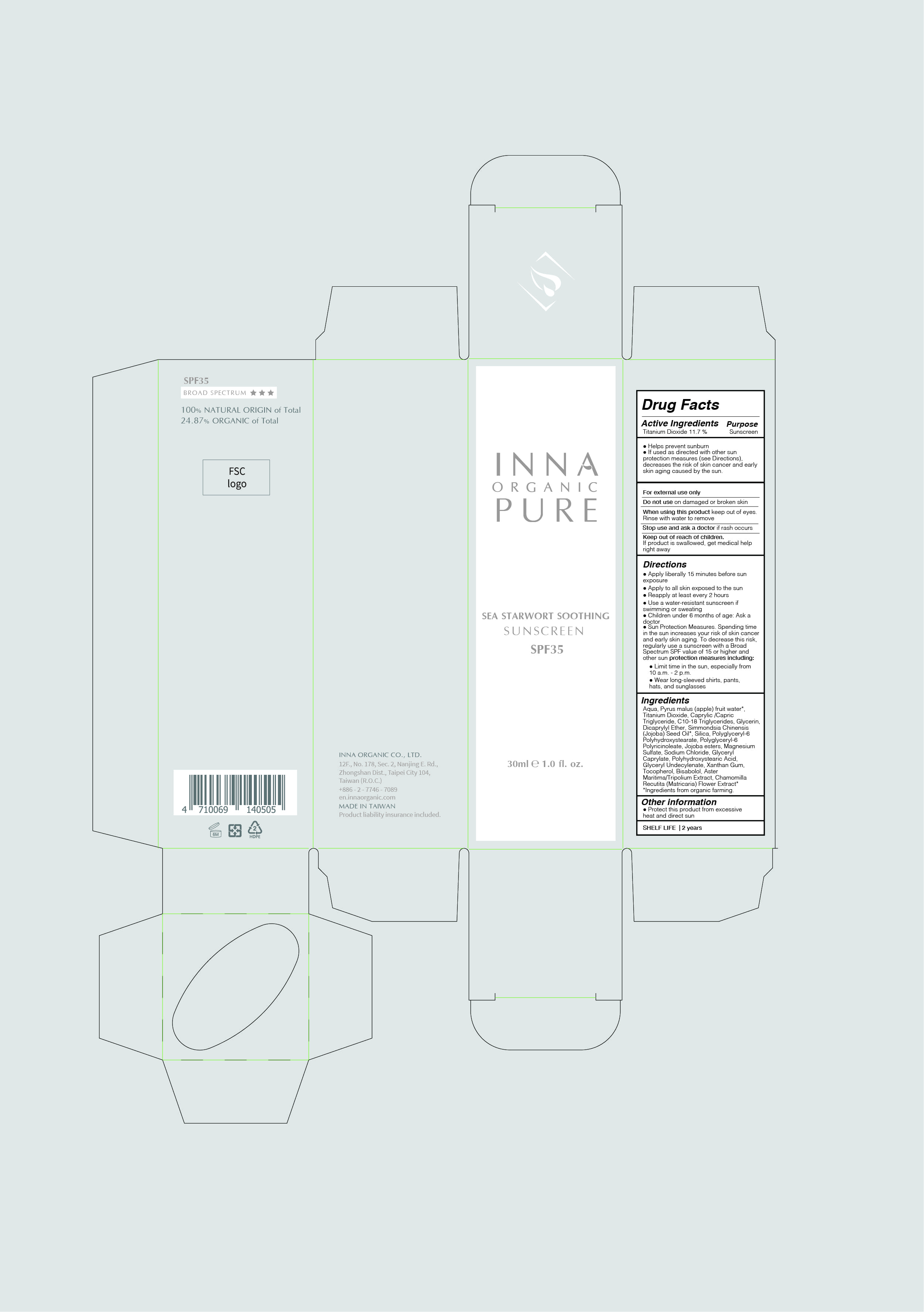 DRUG LABEL: Sea Starwort Soothing Sunscreen SPF 35
NDC: 75391-002 | Form: LOTION
Manufacturer: CU LIFESTYLE LLC
Category: otc | Type: HUMAN OTC DRUG LABEL
Date: 20200422

ACTIVE INGREDIENTS: TITANIUM DIOXIDE 2.91 mg/30 mL
INACTIVE INGREDIENTS: SODIUM CHLORIDE; C10-18 TRIGLYCERIDES; MEDIUM-CHAIN TRIGLYCERIDES; POLYHYDROXYSTEARIC ACID (2300 MW); SIMMONDSIA CHINENSIS SEED; GLYCERYL CAPRYLATE; WATER; .ALPHA.-BISABOLOL, (+/-)-; MAGNESIUM SULFATE HEPTAHYDRATE; GLYCERIN; .ALPHA.-TOCOPHEROL, DL-; HYDROGENATED JOJOBA OIL, RANDOMIZED; SILICON DIOXIDE; DICAPRYLYL ETHER; XANTHAN GUM; APPLE FRUIT OIL

PACKAGE LABEL

Sea Starwort Soothing Sunscreen SPF 35

30 ml 1.0 fl. oz.

Drug Facts

Active Ingredients

Titanium Dioxide 9.7 %

Purpose : Sunscreen

Uses

● Helps prevent sunburn

● If used as directed with other sun protection measures (see Directions), decreases the risk of skin cancer and early skin aging caused by the sun

Warnings

●For external use only

●Do not use on damaged or broken skin

●When using this product keep out of eyes. Rinse with water to remove

●Stop use and ask a doctor if rash occurs

●Keep out of reach of children. If swallowed, get medical help or contact a Poison Control Center right away

Directions

● Apply liberally 15 minutes before sun exposure

● Apply to all skin exposed to the sun

● Reapply at least every 2 hours

● Use a water-resistant sunscreen if swimming or sweating

● Children under 6 months of age: Ask a doctor

● Sun Protection Measures: Spending time in the sun increases your risk of skin cancer and early skin aging. To decrease this risk, regularly use a sunscreen with a Broad Spectrum SPF value of 15 or higher and other sun protection measures including:

● Limit time in the sun, especially from 10 a.m. - 2 p.m.

● Wear long-sleeved shirts, pants, hats, and sunglasses

Ingredients

Aqua, Pyrus malus (apple) fruit water*, Titanium Dioxide, Caprylic /Capric Triglyceride, C10-18 Triglycerides, Glycerin, Dicaprylyl Ether, Simmondsia Chinensis (Jojoba) Seed Oil*, Silica, Polyglyceryl-6 Polyhydroxystearate, Polyglyceryl-6 Polyricinoleate, Jojoba esters, Magnesium Sulfate, Sodium Chloride, Glyceryl Caprylate, Polyhydroxystearic Acid, Glyceryl Undecylenate, Xanthan Gum, Tocopherol, Bisabolol, Aster Maritima/Tripolium Extract, Chamomilla Recutita (Matricaria) Flower Extract*

*Ingredients from organic farming.

Other Information

● Protect the product in this container from excessive heat and direct sun

SHELF LIFE | 2 years

INNA ORGANIC CO., LTD.

12F., No. 178, Sec, 2, Nanjing E. Rd., Zhongshan Dist., Taipei City 104, Taiwan (R.O.C)

+886 -2 – 7746 - 7089

en.innaorganic.com

Made in Taiwan | Product liability insurance included.